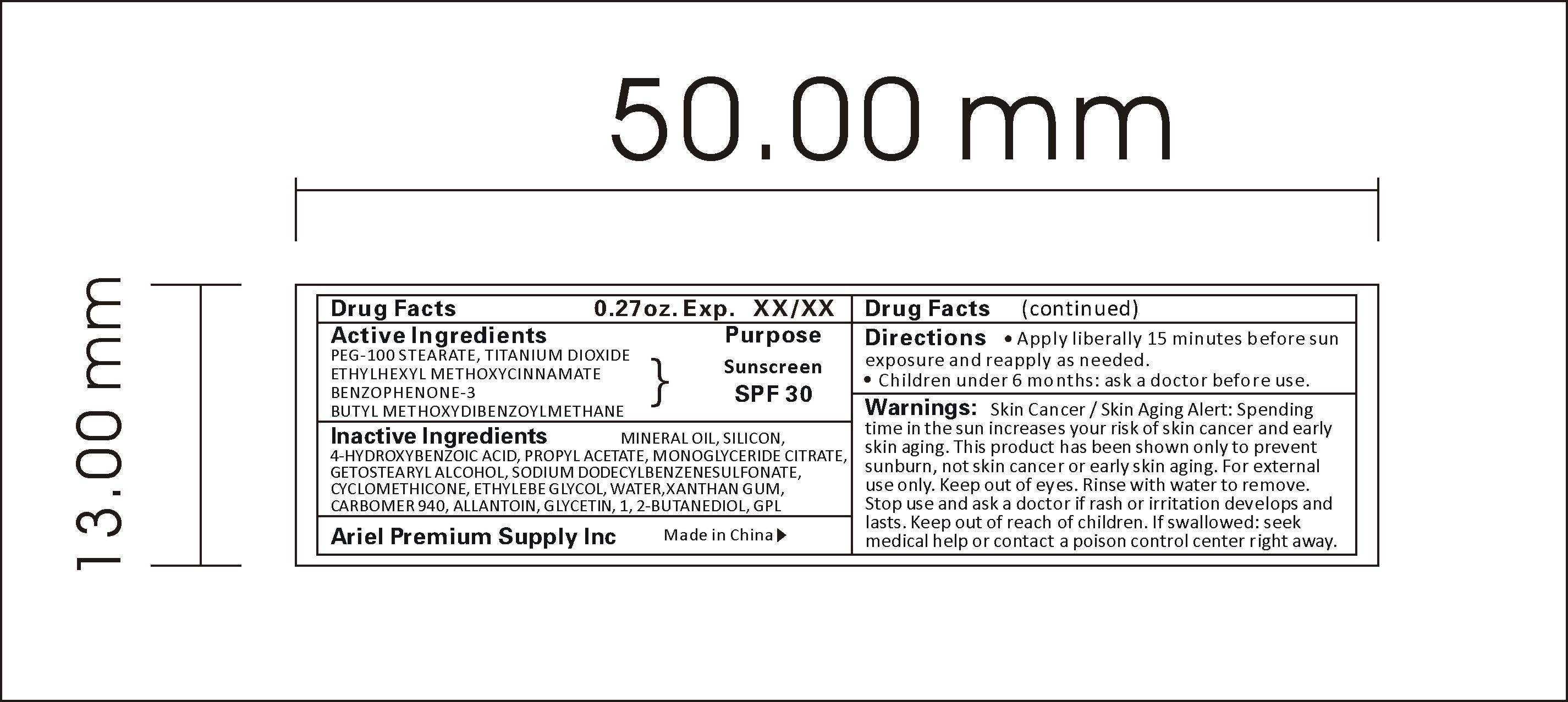 DRUG LABEL: Sunscreen SPF30
NDC: 47993-216 | Form: LIQUID
Manufacturer: NINGBO JIANGBEI OCEAN STAR TRADING CO.,LTD
Category: otc | Type: HUMAN OTC DRUG LABEL
Date: 20180118

ACTIVE INGREDIENTS: PEG-100 STEARATE 2.5 g/100 g; TITANIUM DIOXIDE 4 g/100 g; ETHYLHEXYL METHOXYCRYLENE 1.25 g/100 g; BENZOPHENONE 0.5 g/100 g; AVOBENZONE 0.75 g/100 g
INACTIVE INGREDIENTS: MINERAL OIL 5 g/100 g; SILICON 1 g/100 g; 4-HYDROXYBENZOIC ACID 0.2 g/100 g; PROPYL ACETATE 0.1 g/100 g; GLYCERYL MONOOLEATE CITRATE 1.5 g/100 g; CETOSTEARYL ALCOHOL 2 g/100 g; SODIUM DODECYLBENZENESULFONATE 5 g/100 g; CYCLOMETHICONE 2 g/100 g; ETHYLENE GLYCOL 0.8 g/100 g; WATER 59.7 g/100 g; XANTHAN GUM 0.25 g/100 g; CARBOMER 940 10 g/100 g; ALLANTOIN 0.3 g/100 g; GLYCERIN 2 g/100 g; 1,2-BUTANEDIOL 3 g/100 g; DMDM HYDANTOIN 0.15 g/100 g

Active Ingredients

Active ingredients--------------purpose

PEG-100 STEARATE------------ Sunscreen SPF30

TITANIUM DIOXIDE

ETHYLHEXYL METHOXYCINNAMATE

BUTYL METHOXYDIBENZOYLMETHANE

Warnings:

Skin Cancer / Skin Aging Alert: Spending time in the sun increases your risk of skin cancer and early skin aging. This product has been shown only to prevent sunburn, not skin cancer or early skin aging. For external use only. Keep out of eyes. Rinse with water to remove. Stop use and ask a doctor if rash or irritation develops and lasts. Keep out of reach of children. If swallowed: seek medical help or contact a poison control center right away.

Directions:

Apply liberally 15 minutes before sun exposure and reapply as need.

KEEP OUT OF REACH OF CHILDREN

Children under 6 months: ask a doctor before use.

Inactive Ingredients:

MINERAL OIL, SILICON, 4-HYDROXYBENZOIC ACID, PROPYL ACETATE, MONOGLYCERIDE CITRATE, GETOSTEARYL ALCOHOL, SODIUM DODECYLBENZENESULFONATE, CYCLOMETHICONE, ETHYLENE GLYCOL, WATER, XANTHAN GUM, CARBOMER 940, ALLANTOIN, GLYCERIN, 1,2-BUTANEDIOL, GPL